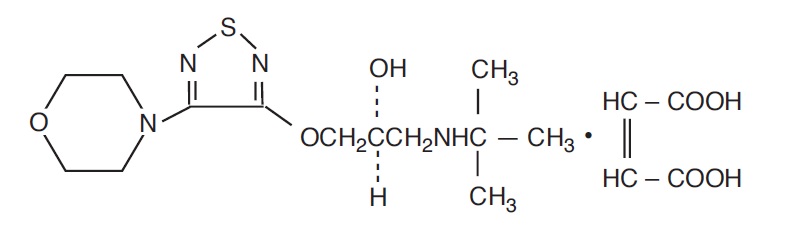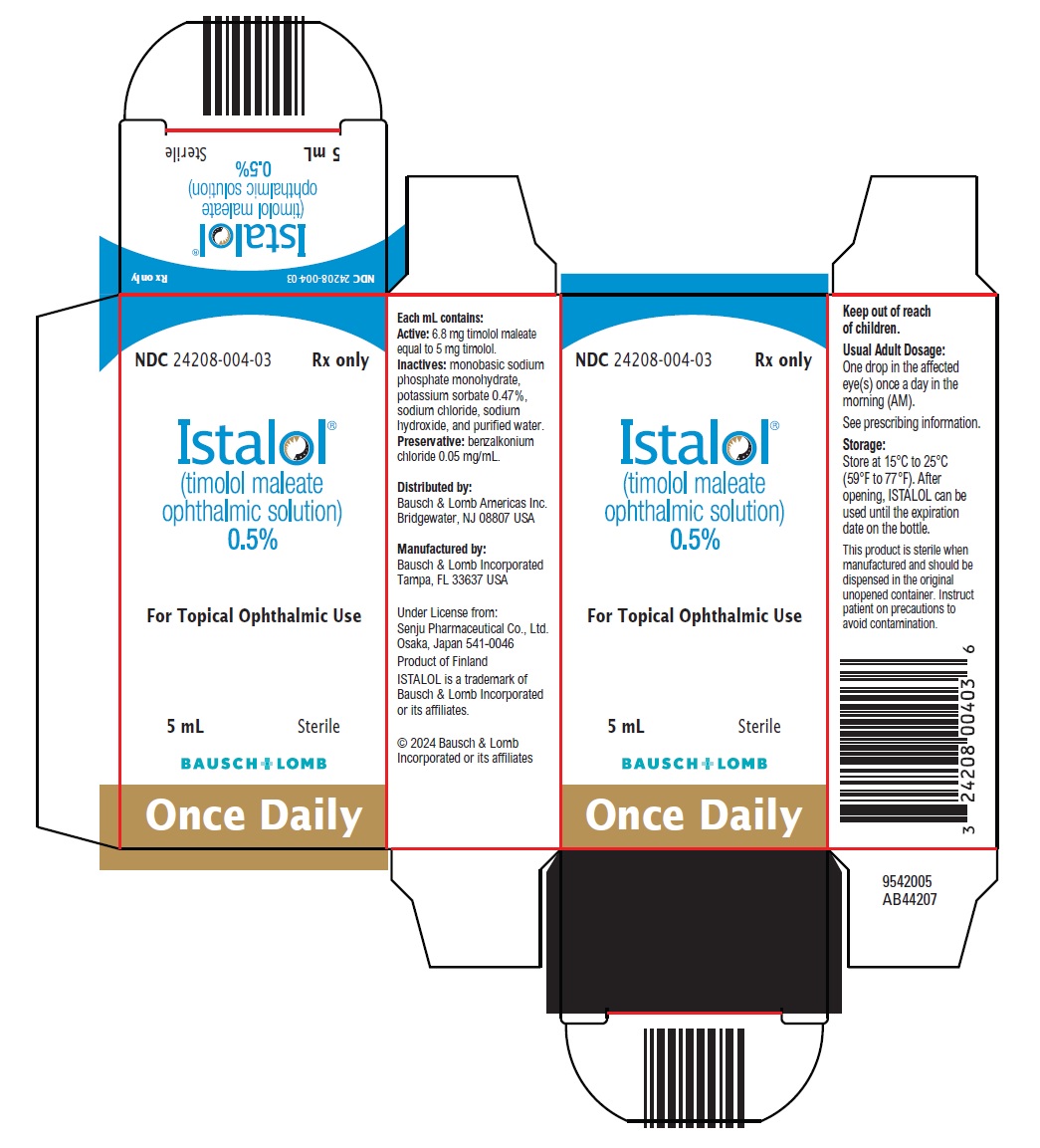 DRUG LABEL: Istalol
NDC: 24208-004 | Form: SOLUTION/ DROPS
Manufacturer: Bausch & Lomb Incorporated
Category: prescription | Type: HUMAN PRESCRIPTION DRUG LABEL
Date: 20241030

ACTIVE INGREDIENTS: TIMOLOL MALEATE 5 mg/1 mL
INACTIVE INGREDIENTS: BENZALKONIUM CHLORIDE 0.05 mg/1 mL; SODIUM PHOSPHATE, MONOBASIC, MONOHYDRATE; POTASSIUM SORBATE; SODIUM CHLORIDE; SODIUM HYDROXIDE; WATER

HIGHLIGHTS OF PRESCRIBING INFORMATION

These highlights do not include all the information needed to use ISTALOL safely and effectively. See full prescribing information for ISTALOL.
ISTALOL®(timolol maleate ophthalmic solution) 0.5%, for topical ophthalmic use
Initial U.S. Approval: 1978

1 INDICATIONS AND USAGE

ISTALOL is a beta adrenergic blocker indicated for the treatment of elevated intraocular pressure in patients with ocular hypertension or open-angle glaucoma. (1)

2 DOSAGE AND ADMINISTRATION

One drop in the affected eye(s) once a day in the morning. (2)

3 DOSAGE FORMS AND STRENGTHS

Ophthalmic solution containing timolol 0.5% (5 mg/mL) (3)

4 CONTRAINDICATIONS

- Bronchial asthma, a history of bronchial asthma, severe chronic obstructive pulmonary disease (4.1, 5.1, 5.3)
- Sinus bradycardia, second or third degree atrioventricular block, overt cardiac failure, cardiogenic shock (4.2, 5.2)
- Hypersensitivity to any component of this product (4.3)

5 WARNINGS AND PRECAUTIONS

- Potentiation of Respiratory Reactions Including Asthma (5.1)
- Cardiac Failure (5.2)
- Obstructive Pulmonary Disease (5.3)
- Increased Reactivity to Allergens (5.4)
- Potentiation of Muscle Weakness (5.5)
- Masking of Hypoglycemic Symptoms in Patients with Diabetes Mellitus (5.6)
- Masking of Thyrotoxicosis (5.7)

6 ADVERSE REACTIONS

The most frequently reported adverse reactions have been burning and stinging upon instillation in 38% of patients treated with ISTALOL. Additional reactions reported with ISTALOL at a frequency of 4% to 10% include: blurred vision, cataract, conjunctival injection, headache, hypertension, infection, itching and decreased visual acuity. (6)

To report SUSPECTED ADVERSE REACTIONS, contact Bausch & Lomb Incorporated at 1-800-553-5340 or FDA at 1-800-FDA-1088 or www.fda.gov/medwatch.

7 DRUG INTERACTIONS

- Concomitant use with systemic beta-blockers may potentiate systemic beta-blockade. (7.1)
- Oral or intravenous calcium antagonists may cause atrioventricular conduction disturbances, left ventricular failure, and hypotension. (7.2)
- Catecholamine-depleting drugs may have additive effects and produce hypotension and/or marked bradycardia. (7.3)
- Digitalis and calcium antagonists may have additive effects in prolonging atrioventricular conduction time. (7.4)
- Potentiated systemic beta-blockade (e.g., decreased heart rate) has been reported during combined treatment with quinidine and timolol. (7.5)

FULL PRESCRIBING INFORMATION

1 INDICATIONS AND USAGE

ISTALOL®is indicated in the treatment of elevated intraocular pressure in patients with ocular hypertension or open-angle glaucoma.

2 DOSAGE AND ADMINISTRATION

One drop of ISTALOL should be administered in the affected eye(s) once a day in the morning (AM).

If more than one topical ophthalmic drug is being used, the drugs should be administered at least five minutes apart.

3 DOSAGE FORMS AND STRENGTHS

Ophthalmic solution containing 0.5% (5 mg/mL) of timolol (6.8 mg/mL of timolol maleate).

4 CONTRAINDICATIONS

4.1 Asthma, COPD

ISTALOL is contraindicated in patients with bronchial asthma; a history of bronchial asthma; severe chronic obstructive pulmonary disease [see Warnings and Precautions (5.1, 5.3)] .

4.2 Sinus Bradycardia, AV Block, Cardiac Failure, Cardiogenic Shock

ISTALOL is contraindicated in patients with sinus bradycardia; second or third degree atrioventricular block; overt cardiac failure; cardiogenic shock [see Warnings and Precautions (5.2)] .

4.3 Hypersensitivity Reactions

ISTALOL is contraindicated in patients who have exhibited a hypersensitivity reaction to any component of this product in the past.

5 WARNINGS AND PRECAUTIONS

5.1 Potentiation of Respiratory Reactions Including Asthma

ISTALOL contains timolol maleate; and although administered topically, it can be absorbed systemically. Therefore, the same adverse reactions found with systemic administration of beta-adrenergic blocking agents may occur with topical administration. For example, severe respiratory reactions and cardiac reactions including death due to bronchospasm in patients with asthma, and rarely death in association with cardiac failure, have been reported following systemic or ophthalmic administration of timolol maleate [see Contraindications (4.1)].

5.2 Cardiac Failure

Sympathetic stimulation may be essential for support of the circulation in individuals with diminished myocardial contractility, and its inhibition of beta-adrenergic receptor blockade may precipitate more severe failure.

In patients without a history of cardiac failure, continued depression of the myocardium with beta-blocking agents over a period of time can, in some cases, lead to cardiac failure. At the first sign or symptom of cardiac failure, ISTALOL should be discontinued [see Contraindications (4.2)].

5.3 Obstructive Pulmonary Disease

Patients with chronic obstructive pulmonary disease (e.g., chronic bronchitis, emphysema) of mild or moderate severity, bronchospastic disease, or a history of bronchospastic disease [other than bronchial asthma or a history of bronchial asthma in which ISTALOL is contraindicated] should, in general, not receive beta-blocking agents, including ISTALOL [see Contraindications (4.1)].

5.4 Increased Reactivity to Allergens

While taking beta-blockers, patients with a history of atopy or a history of severe anaphylactic reactions to a variety of allergens may be more reactive to repeated accidental, diagnostic, or therapeutic challenge with such allergens. Such patients may be unresponsive to the usual doses of epinephrine used to treat anaphylactic reactions.

5.5 Potentiation of Muscle Weakness

Beta-adrenergic blockade has been reported to potentiate muscle weakness consistent with certain myasthenic symptoms (e.g., diplopia, ptosis, and generalized weakness). Timolol has been reported rarely to increase muscle weakness in some patients with myasthenia gravis or myasthenic symptoms.

5.6 Masking of Hypoglycemic Symptoms in Patients with Diabetes Mellitus

Beta-adrenergic blocking agents should be administered with caution in patients subject to spontaneous hypoglycemia or to diabetic patients (especially those with labile diabetes) who are receiving insulin or oral hypoglycemic agents. Beta-adrenergic receptor blocking agents may mask the signs and symptoms of acute hypoglycemia.

5.7 Masking of Thyrotoxicosis

Beta-adrenergic blocking agents may mask certain clinical signs (e.g., tachycardia) of hyperthyroidism. Patients suspected of developing thyrotoxicosis should be managed carefully to avoid abrupt withdrawal of beta-adrenergic blocking agents that might precipitate a thyroid storm.

5.8 Contamination of Topical Ophthalmic Products After Use

There have been reports of bacterial keratitis associated with the use of multiple-dose containers of topical ophthalmic products. These containers had been inadvertently contaminated by patients who, in most cases, had a concurrent corneal disease or a disruption of the ocular epithelial surface [see Patient Counseling Information (17)].

5.9 Impairment of Beta-adrenergically Mediated Reflexes During Surgery

The necessity or desirability of withdrawal of beta-adrenergic blocking agents prior to major surgery is controversial. Beta-adrenergic receptor blockade impairs the ability of the heart to respond to beta-adrenergically mediated reflex stimuli. This may augment the risk of general anesthesia in surgical procedures. Some patients receiving beta-adrenergic receptor blocking agents have experienced protracted severe hypotension during anesthesia. Difficulty in restarting and maintaining the heartbeat has also been reported. For these reasons, in patients undergoing elective surgery, some authorities recommend gradual withdrawal of beta-adrenergic receptor blocking agents. If necessary during surgery, the effects of beta-adrenergic blocking agents may be reversed by sufficient doses of adrenergic agonists.

5.10 Angle-Closure Glaucoma

In patients with angle-closure glaucoma, the immediate objective of treatment is to reopen the angle. This may require constricting the pupil. Timolol maleate has little or no effect on the pupil. ISTALOL should not be used alone in the treatment of angle-closure glaucoma.

5.11 Cerebrovascular Insufficiency

Because of potential effects of beta-adrenergic blocking agents on blood pressure and pulse, these agents should be used with caution in patients with cerebrovascular insufficiency. If signs or symptoms suggesting reduced cerebral blood flow develop following initiation of therapy with ISTALOL, alternative therapy should be considered.

5.12 Choroidal Detachment

Choroidal detachment after filtration procedures has been reported with the administration of aqueous suppressant therapy (e.g., timolol).

5.13 Contact Lens Use

ISTALOL contains benzalkonium chloride, an anti-microbial preservative which may be absorbed by soft contact lenses. Contact lenses should be removed prior to administration of the solution. Lenses may be reinserted 15 minutes following ISTALOL administration.

6 ADVERSE REACTIONS

6.1 Clinical Trials Experience

Because clinical trials are conducted under widely varying conditions, adverse reaction rates observed in the clinical trials of a drug cannot be directly compared to rates in the clinical trials of another drug and may not reflect the rates observed in practice.

The most frequently reported adverse reactions have been burning and stinging upon instillation in 38% of patients treated with ISTALOL. Additional reactions reported with ISTALOL at a frequency of 4% to 10% include: blurred vision, cataract, conjunctival injection, headache, hypertension, infection, itching and decreased visual acuity.

The following additional adverse reactions have been reported less frequently with ocular administration of this or other timolol maleate formulations.

Timolol (Ocular Administration)

Body as a Whole:Asthenia/fatigue and chest pain; Cardiovascular:Bradycardia, arrhythmia, hypotension, syncope, heart block, cerebral vascular accident, cerebral ischemia, cardiac failure, worsening of angina pectoris, palpitation, cardiac arrest, pulmonary edema, edema, claudication, Raynaud’s phenomenon and cold hands and feet; Digestive:Nausea, diarrhea, dyspepsia, anorexia, and dry mouth; Immunologic:Systemic lupus erythematosus; Nervous System/Psychiatric:Dizziness, increase in signs and symptoms of myasthenia gravis, paresthesia, somnolence, insomnia, nightmares, behavioral changes and psychic disturbances including depression, confusion, hallucinations, anxiety, disorientation, nervousness and memory loss; Skin:Alopecia and psoriasiform rash or exacerbation of psoriasis; Hypersensitivity:Signs and symptoms of systemic allergic reactions, including angioedema, urticaria, and localized and generalized rash; Respiratory:Bronchospasm (predominantly in patients with pre-existing bronchospastic disease), respiratory failure, dyspnea, nasal congestion, cough and upper respiratory infections; Endocrine:Masked symptoms of hypoglycemia in diabetic patients [see Warnings and Precautions (5.6)]; Special Senses: Signs and symptoms of ocular irritation including conjunctivitis, blepharitis, keratitis, ocular pain, discharge (e.g., crusting), foreign body sensation, itching and tearing, and dry eyes; ptosis, decreased corneal sensitivity; cystoid macular edema; visual disturbances including refractive changes and diplopia; pseudopemphigoid; choroidal detachment following filtration surgery [see Warnings and Precautions (5.12)]; Urogenital: Retroperitoneal fibrosis, decreased libido, impotence, and Peyronie’s disease.

6.2 Postmarketing Experience

The following adverse reactions have been identified during postapproval use of ISTALOL. Because these reactions are reported voluntarily from a population of uncertain size, it is not always possible to reliably estimate their frequency or establish a causal relationship to drug exposure.

Oral Timolol/Oral Beta-Blockers

The following additional adverse effects have been reported in clinical experience with ORAL timolol maleate or other ORAL beta-blocking agents and may be considered potential effects of ophthalmic timolol maleate: Allergic:Erythematous rash, fever combined with aching and sore throat, laryngospasm with respiratory distress; Body as a Whole:Extremity pain, decreased exercise tolerance, weight loss; Cardiovascular:Worsening of arterial insufficiency, vasodilatation; Digestive:Gastrointestinal pain, hepatomegaly, vomiting, mesenteric arterial thrombosis, ischemic colitis; Hematologic:Nonthrombocytopenic purpura; thrombocytopenic purpura, agranulocytosis; Endocrine:Hyperglycemia, hypoglycemia; Skin:Pruritus, skin irritation, increased pigmentation, sweating; Musculoskeletal:Arthralgia; Nervous System/Psychiatric:Vertigo, local weakness, diminished concentration, reversible mental depression progressing to catatonia, an acute reversible syndrome characterized by disorientation for time and place, emotional lability, slightly clouded sensorium and decreased performance on neuropsychometrics; Respiratory:Rales, bronchial obstruction; Urogenital:Urination difficulties.

7 DRUG INTERACTIONS

7.1 Beta-Adrenergic Blocking Agents

Patients who are receiving a beta-adrenergic blocking agent orally and ISTALOL should be observed for potential additive effects of beta-blockade, both systemic and on intraocular pressure. The concomitant use of two topical beta-adrenergic blocking agents is not recommended.

7.2 Calcium Antagonists

Caution should be used in the co-administration of beta-adrenergic blocking agents, such as ISTALOL, and oral or intravenous calcium antagonists because of possible atrioventricular conduction disturbances, left ventricular failure, and hypotension. In patients with impaired cardiac function, co-administration should be avoided.

7.3 Catecholamine-Depleting Drugs

Close observation of the patient is recommended when a beta-blocker is administered to patients receiving catecholamine-depleting drugs such as reserpine, because of possible additive effects and the production of hypotension and/or marked bradycardia, which may result in vertigo, syncope, or postural hypotension.

7.4 Digitalis and Calcium Antagonists

The concomitant use of beta-adrenergic blocking agents with digitalis and calcium antagonists may have additive effects in prolonging atrioventricular conduction time.

7.5 CYP2D6 Inhibitors

Potentiated systemic beta-blockade (e.g., decreased heart rate) has been reported during combined treatment with CYP2D6 inhibitors (e.g., quinidine) and timolol.

7.6 Clonidine

Oral beta-adrenergic blocking agents may exacerbate the rebound hypertension which can follow the withdrawal of clonidine. There have been no reports of exacerbation of rebound hypertension with ophthalmic timolol maleate.

8 USE IN SPECIFIC POPULATIONS

8.1 Pregnancy

Risk Summary

There are no adequate and well-controlled studies in pregnant women with timolol maleate to inform a drug-associated risk. Administration of oral timolol maleate to pregnant mice, rats and rabbits did not produce teratogenicity at clinically relevant systemic exposures (see Data).Because animal reproductive studies are not always predictive of human response, ISTALOL should be used during pregnancy only if the potential benefit justifies the potential risk to the fetus.

In the U.S. general population, the estimated background risk of major birth defects and miscarriage in clinically recognized pregnancies is 2-4% and 15-20%, respectively.

Data

Animal Data

Teratogenicity studies with timolol in pregnant mice, rats, and rabbits at oral doses up to 50 mg/kg/day (7,000 times the systemic exposure following the maximum recommended human ophthalmic dose) demonstrated no evidence of fetal malformations. Although delayed fetal ossification was observed at this dose in rats, there were no adverse effects on postnatal development of offspring. Doses of 1,000 mg/kg/day (142,000 times the systemic exposure following the maximum recommended human ophthalmic dose) were maternally toxic in mice and resulted in an increased number of fetal resorptions. Increased fetal resorptions were also seen in rabbits at doses of 14,000 times the systemic exposure following the maximum recommended human ophthalmic dose without apparent maternal toxicity.

8.2 Lactation

Risk Summary

Timolol has been detected in human milk following oral and ophthalmic drug administration. The developmental and health benefits of breastfeeding should be considered along with the mother’s clinical need for ISTALOL and any potential adverse effects on the breastfed child from ISTALOL.

8.4 Pediatric Use

The safety and effectiveness of ISTALOL in pediatric patients have not been established.

8.5 Geriatric Use

No overall differences in safety or effectiveness have been observed between elderly and younger patients.

10 OVERDOSAGE

There have been reports of inadvertent overdosage with ISTALOL resulting in systemic effects similar to those seen with systemic beta-adrenergic blocking agents such as dizziness, headache, shortness of breath, bradycardia, bronchospasm, and cardiac arrest.

An in vitro hemodialysis study, using^14C timolol added to human plasma or whole blood, showed that timolol was readily dialyzed from these fluids; however, a study of patients with renal failure showed that timolol did not dialyze readily.

11 DESCRIPTION

ISTALOL (timolol maleate ophthalmic solution) 0.5% is a non-selective beta-adrenergic receptor blocking agent for topical ophthalmic use. Its chemical name is (-)-1-(tert-butylamino)-3-[(4-morpholino-1,2,5-thiadiazol-3-yl)oxy]-2-propanol maleate (1:1) (salt). Timolol maleate possesses an asymmetric carbon atom in its structure and is provided as the levo-isomer.

Its molecular formula is C13H24N4O3S-C4H4O4and its structural formula is:

Timolol maleate has a molecular weight of 432.49. It is a white, odorless, crystalline powder which is soluble in water, methanol, and alcohol. ISTALOL is stable at room temperature. ISTALOL ophthalmic solution is supplied as a sterile, isotonic, buffered, aqueous solution of timolol maleate in a single strength. It has a pH of 6.5-7.5 and an osmolality of 275-330 mOsm/kg.

Each mL of ISTALOL contains the active ingredient 5 mg of timolol (6.8 mg of timolol maleate) with the inactive ingredients benzalkonium chloride (0.05 mg/mL), monobasic sodium phosphate monohydrate, potassium sorbate 0.47%, sodium chloride, sodium hydroxide, and purified water.

12 CLINICAL PHARMACOLOGY

12.1 Mechanism of Action

Timolol maleate is a beta1and beta2(non-selective) adrenergic receptor blocking agent that does not have significant intrinsic sympathomimetic, direct myocardial depressant, or local anesthetic (membrane-stabilizing) activity.

Beta-adrenergic receptor blockade reduces cardiac output in both healthy subjects and patients with heart disease. In patients with severe impairment of myocardial function, beta-adrenergic receptor blockade may inhibit the stimulatory effect of the sympathetic nervous system necessary to maintain adequate cardiac function.

Beta-adrenergic receptor blockade in the bronchi and bronchioles results in increased airway resistance from unopposed parasympathetic activity. Such an effect in patients with asthma or other bronchospastic conditions is potentially dangerous.

ISTALOL ophthalmic solution, when applied topically on the eye, has the action of reducing elevated as well as normal intraocular pressure, whether or not accompanied by glaucoma. Elevated intraocular pressure is a major risk factor in the pathogenesis of glaucomatous visual field loss. The higher the level of intraocular pressure, the greater the likelihood of glaucomatous visual field loss and optic nerve damage.

The onset of reduction in intraocular pressure following administration of ISTALOL can usually be detected within one-half hour after a single dose. The maximum effect usually occurs in one to two hours and significant lowering of intraocular pressure can be maintained for periods as long as 24 hours with a single dose. Repeated observations over a period of one year indicate that the intraocular pressure lowering effect of ISTALOL is well maintained.

The precise mechanism of the ocular hypotensive action of ISTALOL is not clearly established at this time. Tonography and fluorophotometry studies in man suggest that its predominant action may be related to reduced aqueous formation. However, in some studies a slight increase in outflow facility was also observed.

12.3 Pharmacokinetics

In a study of plasma drug concentration in 12 healthy subjects, the systemic exposure to timolol was determined following twice daily administration of ISTALOL (exaggerated regimen) for eight days. With ISTALOL, mean plasma concentrations of timolol were 0.68 ng/mL and 0.88 ng/mL two hours after the first dose and the dose on the eighth day, respectively.

13 NONCLINICAL TOXICOLOGY

13.1 Carcinogenesis, Mutagenesis, Impairment of Fertility

Carcinogenesis

In a two-year study of timolol maleate administered orally to rats, there was a statistically significant increase in the incidence of adrenal pheochromocytomas in male rats administered 300 mg/kg/day (approximately 42,000 times the systemic exposure following the maximum recommended human ophthalmic dose). Similar differences were not observed in rats administered oral doses equivalent to approximately 14,000 times the maximum recommended human ophthalmic dose.

In a lifetime oral study in mice, there were statistically significant increases in the incidence of benign and malignant pulmonary tumors, benign uterine polyps and mammary adenocarcinomas in female mice at 500 mg/kg/day, (approximately 71,000 times the systemic exposure following the maximum recommended human ophthalmic dose), but not at 5 or 50 mg/kg/day (approximately 700 or 7,000, respectively, times the systemic exposure following the maximum recommended human ophthalmic dose). In a subsequent study in female mice, in which post-mortem examinations were limited to the uterus and the lungs, a statistically significant increase in the incidence of pulmonary tumors was again observed at 500 mg/kg/day.

The increased occurrence of mammary adenocarcinomas was associated with elevations in serum prolactin which occurred in female mice administered oral timolol at 500 mg/kg/day, but not at doses of 5 or 50 mg/kg/day. An increased incidence of mammary adenocarcinomas in rodents has been associated with administration of several other therapeutic agents that elevate serum prolactin, but no correlation between serum prolactin levels and mammary tumors has been established in humans. Furthermore, in adult human female subjects who received oral dosages of up to 60 mg of timolol maleate (the maximum recommended human oral dosage), there were no clinically meaningful changes in serum prolactin.

Mutagenesis

Timolol maleate was devoid of mutagenic potential when tested in vivo (mouse) in the micronucleus test and cytogenetic assay (doses up to 800 mg/kg) and in vitro in a neoplastic cell transformation assay (up to 100 mcg/mL). In Ames tests the highest concentrations of timolol employed, 5,000 or 10,000 mcg/plate, were associated with statistically significant elevations of revertants observed with tester strain TA100 (in seven replicate assays), but not in the remaining three strains. In the assays with tester strain TA100, no consistent dose response relationship was observed, and the ratio of test to control revertants did not reach 2. A ratio of 2 is usually considered the criterion for a positive Ames test.

Impairment of Fertility

Reproduction and fertility studies in rats demonstrated no adverse effect on male or female fertility at doses up to 21,000 times the systemic exposure following the maximum recommended human ophthalmic dose.

14 CLINICAL STUDIES

In a controlled, double-masked, parallel study in 332 patients with untreated intraocular pressures of 22 mm Hg or greater, ISTALOL 0.5% administered once daily (AM) was equivalent to timolol maleate ophthalmic solution 0.5% administered twice daily. In both groups, mean intraocular pressure decreased from 25 mm Hg at baseline to 18 mm Hg at peak and 19 mm Hg at trough. ISTALOL was generally well tolerated, and 3% of patients had treatment discontinued for adverse events judged related to treatment. There was a slight decrease in cardiovascular function consistent with known systemic absorption of a β-adrenoceptor antagonist.

16 HOW SUPPLIED/STORAGE AND HANDLING

ISTALOL (timolol maleate ophthalmic solution) 0.5% is supplied in white LDPE bottles with 15 mm PP yellow caps and 15 mm LLDPE white dropper tips as follows:

NDC 24208-004-03 5 mL in 10 mL container

NDC 24208-004-01 2.5 mL in 7.5 mL container

Storage:

Store at 15ºC to 25ºC (59ºF to 77ºF). After opening, ISTALOL can be used until the expiration date on the bottle.

17 PATIENT COUNSELING INFORMATION

Asthma, COPD, Sinus Bradycardia, AV Block, Cardiac Failure, Cardiogenic Shock

Patients with bronchial asthma, a history of bronchial asthma, severe chronic obstructive pulmonary disease (COPD), sinus bradycardia, second or third degree atrioventricular block, or cardiac failure should be advised not to use ISTALOL [see Contraindications (4.1, 4.2)].

Avoiding Contamination of the Product

Instruct patients that ocular solutions, if handled improperly or if the tip of the dispensing container contacts the eye or surrounding structures, can become contaminated by common bacteria known to cause ocular infections. Serious damage to the eye and subsequent loss of vision may result from using contaminated solutions [see Warnings and Precautions (5.8)].

When to Seek Physician Advice

Advise patients that if they have ocular surgery or develop an intercurrent ocular condition (e.g., trauma or infection), they should immediately seek their physician’s advice concerning the continued use of the present multiple-dose container.

Concomitant Topical Ophthalmic Medications

Advise patients that if more than one topical ophthalmic drug is being used, the drugs should be administered at least five minutes apart.

Contact Lens Use

Advise patients that ISTALOL contains benzalkonium chloride, an anti-microbial preservative, which may be absorbed by soft contact lenses. Contact lenses should be removed prior to administration of the solution. Lenses may be reinserted 15 minutes following ISTALOL administration.

Distributed by:

Bausch & Lomb Americas Inc.

Bridgewater, NJ 08807 USA

Manufactured by:

Bausch & Lomb Incorporated

Tampa, FL 33637 USA

Under License from:

Senju Pharmaceutical Co., Ltd.

Osaka, Japan 541-0046

ISTALOL is a trademark of Bausch & Lomb Incorporated or its affiliates.

© 2024 Bausch & Lomb Incorporated or its affiliates

9733102 (Folded)

9733202 (Flat)

PACKAGE/LABEL PRINCIPAL DISPLAY PANEL

NDC24208-004-03 Rx only

Istalol®
(timolol maleate
ophthalmic solution)
0.5%

For Topical Ophthalmic Use

5mLSterile

BAUSCH + LOMB

Once Daily

9542005
AB44207